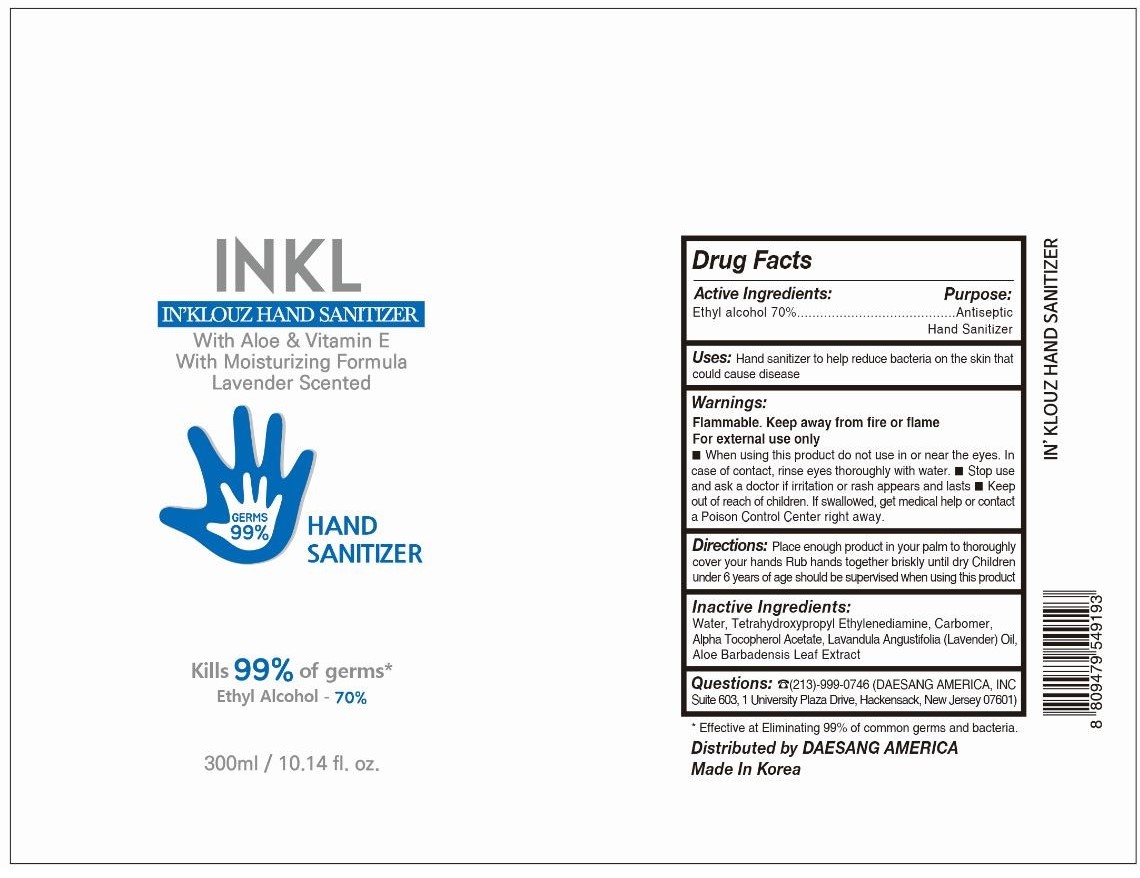 DRUG LABEL: INKLOUZ HAND SANITIZER
NDC: 73863-200 | Form: LIQUID
Manufacturer: MJ Cosmetic Co., Ltd.
Category: otc | Type: HUMAN OTC DRUG LABEL
Date: 20200727

ACTIVE INGREDIENTS: ALCOHOL 70 mL/100 mL
INACTIVE INGREDIENTS: LAVENDER OIL; WATER; BUTYLENE GLYCOL; HYALURONATE SODIUM; 1,2-HEXANEDIOL; GLYCERIN

Active Ingredient

Ethyl alcohol 70% v/v

Purpose

Antiseptic

Uses

Hand sanitizer to help reduce bacteria potentially can cause disease. For use when soap and water are not available.

Warnings

For external use only. Flammable. Keep away from heat or flame.

Do not use

- In children less than 2 month of age
- On open skin wounds

When using this product, do not use in or near the eyes. In case of contact, rinse eyes thoroughly with water.

STOP USE

Discontinue if irritation or redness develops. If condition persists for more than 72 hours, consult a doctor.

Keep out of reach of children. If swallowed, get medical help or contact Poison Control Center right away.

Directions

- Place enough product in your palm to thoroughly cover your hands.
- Rub hands together until dry.
- Supervise children under 6 years of age when using this product to avoid swallowing.

Other information

- Store between 15-30˚C (59-86˚F)
- Avoid freezing and excessive heat above 40˚C (104˚F)
- May discolor certain fabrics.

Inactive Ingredients

Water, Butylene Glycol, Glycerin, Lavandula Angustifolia (Lavender) Oil, 1,2-Hexanediol, Sodium Hyaluronate

Questions

☎323-728-8555